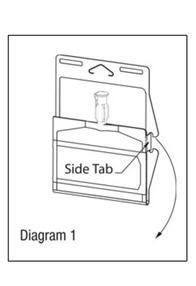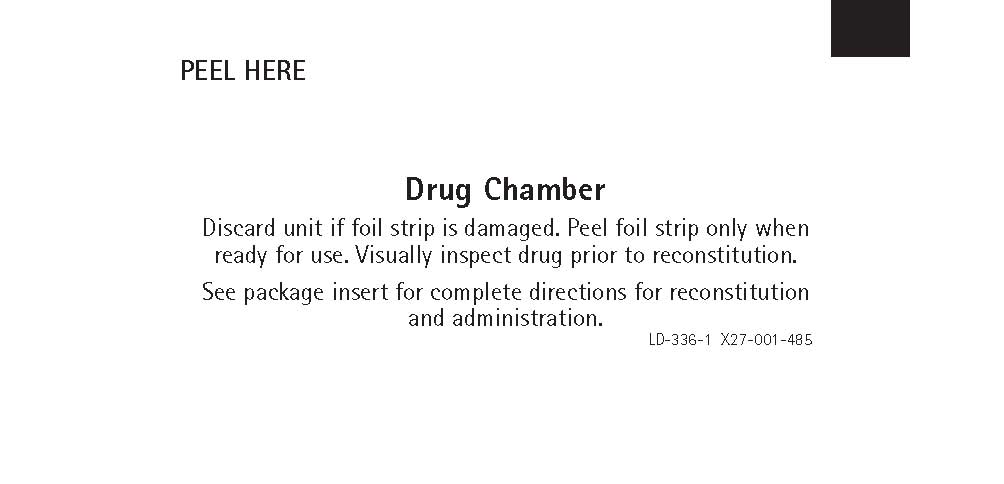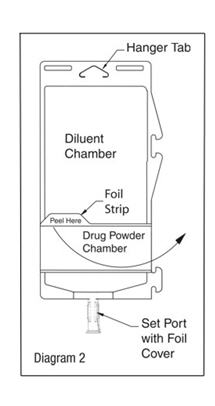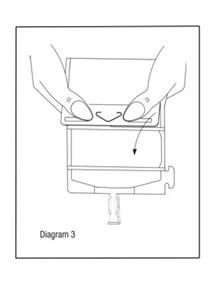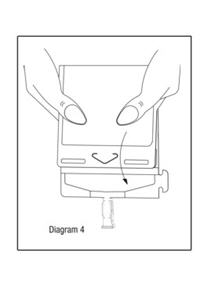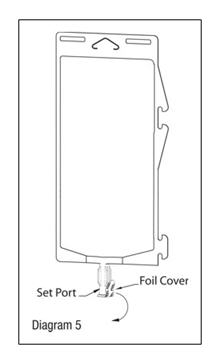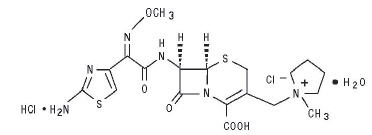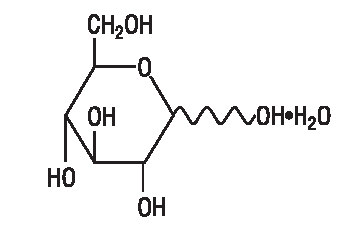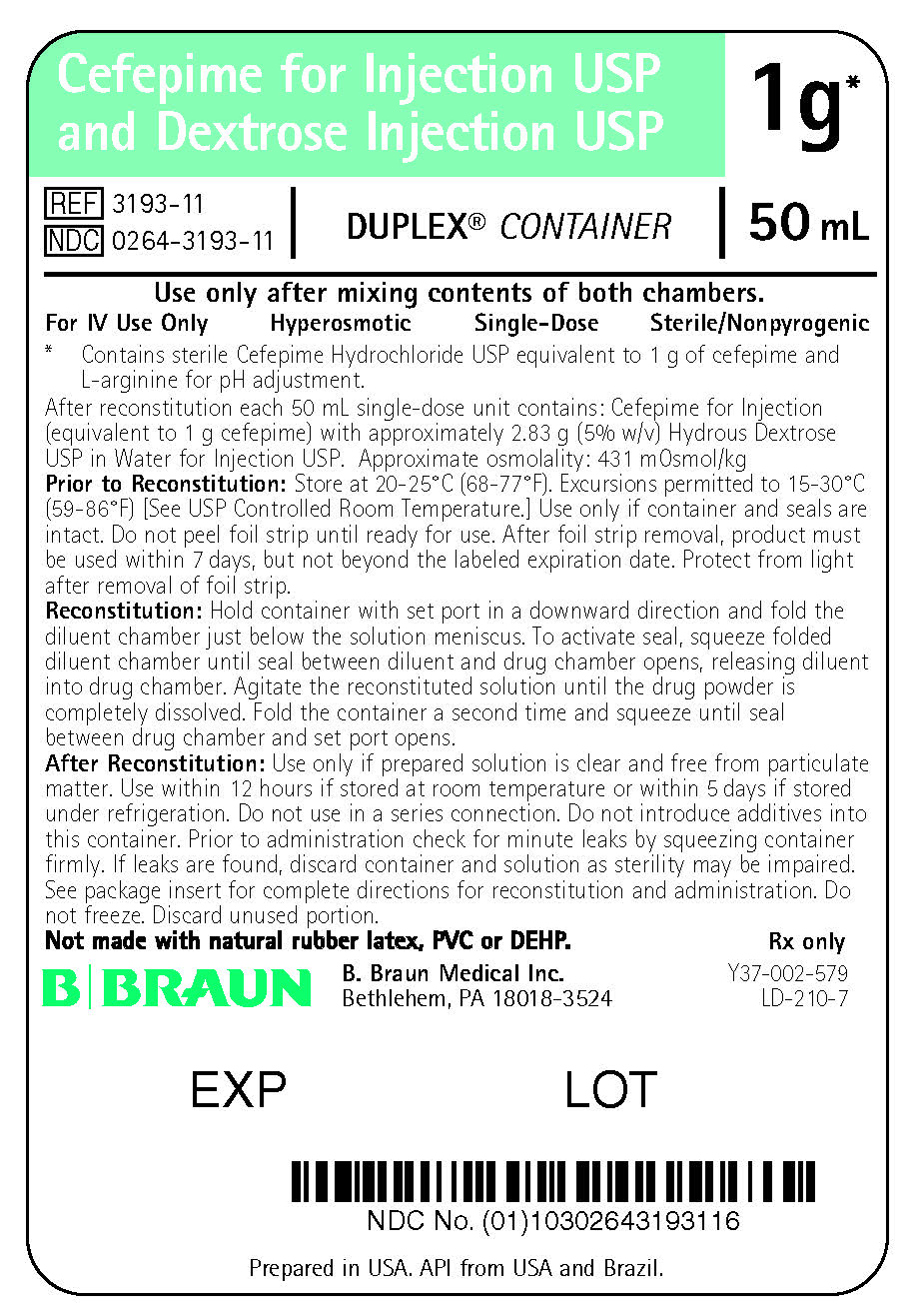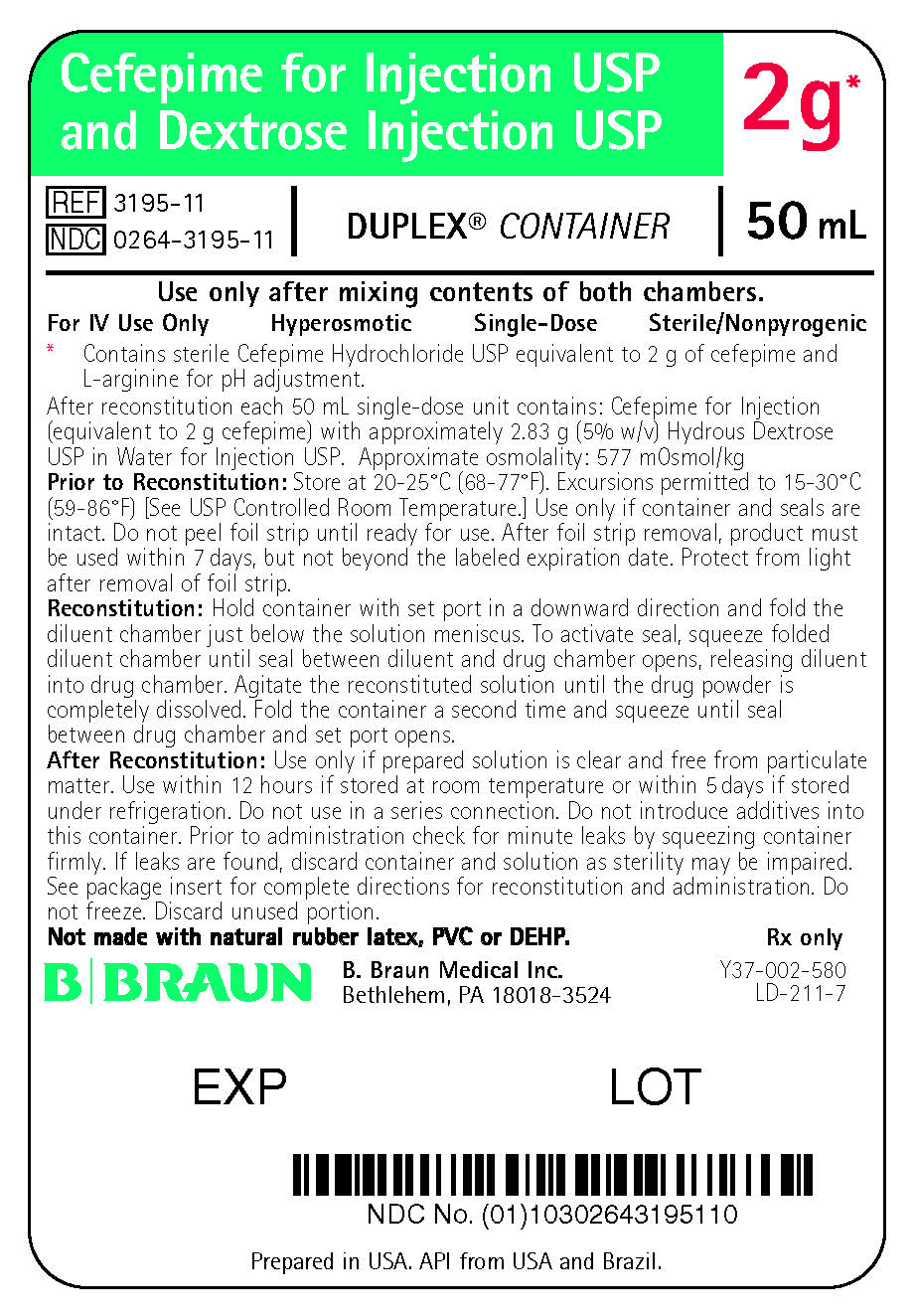 DRUG LABEL: CEFEPIME HYDROCHLORIDE AND DEXTROSE
NDC: 0264-3193 | Form: INJECTION, SOLUTION
Manufacturer: B. Braun Medical Inc.
Category: prescription | Type: HUMAN PRESCRIPTION DRUG LABEL
Date: 20220318

ACTIVE INGREDIENTS: CEFEPIME HYDROCHLORIDE 1 g/50 mL
INACTIVE INGREDIENTS: DEXTROSE MONOHYDRATE 2.83 g/50 mL; WATER

HIGHLIGHTS OF PRESCRIBING INFORMATION

These highlights do not include all the information needed to use CEFEPIME FOR INJECTION AND DEXTROSE INJECTION safely and effectively. See full prescribing information for CEFEPIME FOR INJECTION AND DEXTROSE INJECTION.
CEFEPIME for injection and DEXTROSE injection, for intravenous use
Initial U.S. Approval: 1996

MICROBIOLOGY

To reduce the development of drug-resistant bacteria and maintain the effectiveness of Cefepime for Injection USP and Dextrose Injection USP and other antibacterial drugs, Cefepime for Injection USP and Dextrose Injection USP should be used only to treat or prevent infections that are proven or strongly suspected to be caused by bacteria. (1)

1 INDICATIONS AND USAGE

Cefepime for Injection and Dextrose Injection is a cephalosporin antibacterial indicated in the treatment of the following infections caused by susceptible strains of the designated microorganisms:

- Pneumonia (1.1)
- Empiric therapy for febrile neutropenic patients (1.2)
- Uncomplicated and complicated urinary tract infections (1.3)
- Uncomplicated skin and skin structure infections (1.4)
- Complicated intra-abdominal infections (used in combination with metronidazole) (1.5)

To reduce the development of drug-resistant bacteria and maintain the effectiveness of Cefepime for Injection and Dextrose Injection and other antibacterial drugs, Cefepime for Injection and Dextrose Injection should be used only to treat or prevent infections that are proven or strongly suspected to be caused by bacteria. (1.6)

2 DOSAGE AND ADMINISTRATION

For intravenous use only administered over approximately 30 minutes. (2)

Use this formulation of cefepime only in adult and pediatric patients who require the entire 1 or 2 gram dose and not any fraction thereof. (2.1, 2.2)

Recommended Dosing Schedule in Adult Patients with CrCL Greater than 60 mL/min (2.1)*
Site and Type of Infection | Dose | Frequency | Duration (days)
Moderate to severe pneumonia [For Pseudomonas aeruginosa, use 2 g IV every 8 hours (2.1)] | 1 or 2 g IV | Every 8-12 hours | 10 days
Empiric therapy for febrile neutropenic patients | 2 g IV | Every 8 hours | 7 days [Or until resolution of neutropenia. (2.1)]
Mild to moderate uncomplicated or complicated urinary tract infections | 0.5 or 1 g IV | Every 12 hours | 7–10 days
Severe uncomplicated or complicated urinary tract infections | 2 g IV | Every 12 hours | 10 days
Moderate to severe uncomplicated skin and skin structure infections | 2 g IV | Every 12 hours | 10 days
Complicated intra-abdominal infections (used in combination with metronidazole) | 2 g IV | Every 8-12 hours | 7–10 days

Pediatric Patients (2 months to 16 years): Recommended Dosage in pediatric patients with CrCl greater than 60 mL/min. (2.2)

- The usual recommended dosage in pediatric patients is 50 mg per kg per dose administered every 12 hours (every 8 hours for febrile neutropenia). (2.2)

- Patient with Renal Impairment: Adjust dose in patients with CrCl less than or equal to 60 mL/min (2.3)

3 DOSAGE FORMS AND STRENGTHS

- Injection: 1 g in 50 mL and 2 g in 50 mL in a DUPLEX® Container (3)

4 CONTRAINDICATIONS

- Patients with known immediate hypersensitivity reactions to cefepime or other cephalosporins, penicillins or other beta-lactam antibacterial drugs. (4)

5 WARNINGS AND PRECAUTIONS

- Hypersensitivity reactions: Cross-hypersensitivity may occur in up to 10% of patients with a history of penicillin allergy. If an allergic reaction occurs, discontinue the drug. (5.1)
- Neurotoxicity: May occur especially in patients with renal impairment administered unadjusted doses. If neurotoxicity associated with Cefepime for Injection and Dextrose Injection occurs, discontinue the drug. (5.2)
- Clostridioides difficile-associated diarrhea (CDAD): Evaluate if diarrhea occurs. (5.3)

6 ADVERSE REACTIONS

- The most common adverse reactions (incidence ≥1%) were local reactions, positive Coombs’ test, decreased phosphorous, increased ALT and AST, increased PT and PTT and rash. (6.1)

- At the highest dose (2 g every 8 hours), incidence of adverse reactions was ≥1% for rash, diarrhea, nausea, vomiting, pruritis, fever, and headache. (6.1)

To report SUSPECTED ADVERSE REACTIONS, contact B. Braun Medical Inc. at 1-800-854-6851 or FDA at 1-800-FDA-1088 or www.fda.gov/medwatch.

7 DRUG INTERACTIONS

- Aminoglycosides: Increased potential of nephrotoxicity and ototoxicity. (7.2)
- Diuretics: Nephrotoxicity has been reported with concomitant administration of cephalosporins with potent diuretics such as furosemide. Monitor renal function. (7.3)

8 USE IN SPECIFIC POPULATIONS

- Geriatric Use: Serious neurologic adverse reactions have occurred in geriatric patients with renal insufficiency given unadjusted doses of cefepime (5.2, 8.5)
- Pediatric use: Safety and efficacy have not been established in patients less than 2 months of age or for use in any pediatric patients with complicated intra-abdominal infections. (8.4)

FULL PRESCRIBING INFORMATION

1 INDICATIONS AND USAGE

1.1 Pneumonia

Cefepime for Injection and Dextrose Injection is indicated for the treatment of pneumonia (moderate to severe) caused by Streptococcus pneumoniae (including cases associated with concurrent bacteremia), Pseudomonas aeruginosa, Klebsiella pneumoniae, or Enterobacter species.

1.2 Empiric Therapy for Febrile Neutropenic Patients

Cefepime for Injection and Dextrose Injection as monotherapy is indicated for empiric treatment of febrile neutropenic patients. In patients at high risk for severe infection (including patients with a history of recent bone marrow transplantation, with hypotension at presentation, with an underlying hematologic malignancy, or with severe or prolonged neutropenia), antimicrobial monotherapy may not be appropriate. Insufficient data exist to support the efficacy of cefepime monotherapy in such patients [see Clinical Studies (14.1)].

1.3 Uncomplicated and Complicated Urinary Tract Infections (including pyelonephritis)

Cefepime for Injection and Dextrose Injection is indicated for uncomplicated and complicated urinary tract infections (including pyelonephritis) caused by Escherichia coli or Klebsiella pneumoniae when the infection is severe, or caused by Escherichia coli, Klebsiella pneumoniae, or Proteus mirabilis when the infection is mild to moderate, including cases associated with concurrent bacteremia with these microorganisms.

1.4 Uncomplicated Skin and Skin Structure Infections

Cefepime for Injection and Dextrose Injection is indicated in the treatment of uncomplicated skin and skin structure infections caused by Staphylococcus aureus (methicillin-susceptible strains only) or Streptococcus pyogenes.

1.5 Complicated Intra-abdominal Infections

Cefepime for Injection and Dextrose Injection is indicated for complicated intra-abdominal infections (used in combination with metronidazole) caused by Escherichia coli, viridans group streptococci, Pseudomonas aeruginosa, Klebsiella pneumoniae, Enterobacter species, or Bacteroides fragilis [see Clinical Studies (14.2)].

1.6 Usage

To reduce the development of drug-resistant bacteria and maintain the effectiveness of Cefepime for Injection and Dextrose Injection and other antibacterial drugs, Cefepime for Injection and Dextrose Injection should be used only to treat or prevent infections that are proven or strongly suspected to be caused by susceptible bacteria. When culture and susceptibility information are available, they should be considered in selecting or modifying antibacterial therapy. In the absence of such data, local epidemiology and susceptibility patterns may contribute to the empiric selection of therapy.

2 DOSAGE AND ADMINISTRATION

2.1 Dosage for Adults

Cefepime for Injection and Dextrose Injection in the DUPLEX® Container should be used only in patients who require the entire 1 or 2 gram dose and not any fraction thereof.

The recommended adult dosages and routes of administration are outlined in Table 1 below for patients with creatinine clearance greater than 60 mL/min. Administer Cefepime for Injection and Dextrose Injection intravenously over approximately 30 minutes.

Table 1: Recommended Dosing Schedule for Cefepime for Injection and Dextrose Injection in Adult Patients with CrCL Greater Than 60 mL/min
Site and Type of Infection | Dose | Frequency | Duration (days)
Adults | Intravenous (IV)
Moderate to Severe Pneumonia due to S. pneumoniae, P. aeruginosa [For P. aeruginosa, use 2 g IV every 8 hours.] , K. pneumoniae, or Enterobacter species | 1-2 g IV | Every 8 to 12 hours | 10
Empiric therapy for febrile neutropenic patients [see Indications and Usage (1) and Clinical Studies (14)] | 2 g IV | Every 8 hours | 7 [or until resolution of neutropenia. In patients whose fever resolves but who remain neutropenic for more than 7 days, the need for continued antimicrobial therapy should be re-evaluated frequently.]
Mild to Moderate Uncomplicated or Complicated Urinary Tract Infections, including pyelonephritis, due to E. coli, K. pneumoniae, or P. mirabilis | 0.5-1 g IV | Every 12 hours | 7 to 10
Severe Uncomplicated or Complicated Urinary Tract Infections, including pyelonephritis, due to E. coli or K. pneumoniae | 2 g IV | Every 12 hours | 10
Moderate to Severe Uncomplicated Skin and Skin Structure Infections due to S. aureus or S. pyogenes | 2 g IV | Every 12 hours | 10
Complicated Intra-abdominal Infections (used in combination with metronidazole) caused by E. coli, viridans group streptococci, P. aeruginosa, K. pneumoniae, Enterobacter species, or B. fragilis. [see Clinical Studies (14)] | 2 g IV | Every 8 to 12 hours | 7 to 10

2.2 Pediatric Patients (2 months up to 16 years)

The maximum dose for pediatric patients should not exceed the recommended adult dose. The usual recommended dosage in pediatric patients up to 40 kg in weight for durations as given above for adults is:

- 50 mg per kg per dose, administered every 12 hours for uncomplicated and complicated urinary tract infections (including pyelonephritis), uncomplicated skin and skin structure infections, and pneumonia (see below).
- For moderate to severe pneumonia due to P. aeruginosa give 50 mg per kg per dose, every 8 hours for febrile neutropenic patients.
- 50 mg per kg per dose, every 8 hours for febrile neutropenic patients.

Cefepime for Injection and Dextrose Injection in the DUPLEX® Container is designed to deliver a 1 g or 2 g dose of cefepime. To prevent unintentional overdose, this product should not be used in pediatric patients who require less than the full adult dose of cefepime.

2.3 Dosage Adjustments in Patients with Renal Impairment

Adult Patients

Adjust the dose of Cefepime for Injection and Dextrose Injection in patients with creatinine clearance less than or equal to 60 mL/min, to compensate for the slower rate of renal elimination. In these patients, the recommended initial dose of Cefepime for Injection and Dextrose Injection should be the same as in patients with CrCL greater than 60 mL/min except in patients undergoing hemodialysis. The recommended doses of Cefepime for Injection and Dextrose Injection in patients with renal impairment are presented in Table 2.

Cefepime for Injection and Dextrose Injection in the DUPLEX® Container should be used only in patients who require the entire 1 or 2 gram dose and not any fraction thereof.

When only serum creatinine is available, the following formula (Cockcroft and Gault equation)^1 may be used to estimate creatinine clearance [see References (15)].

The serum creatinine should represent a steady state of renal function:

Males: | Creatinine Clearance (mL/min) = | Weight (kg) × (140-age)
 |  | 72 × serum creatinine (mg/dL)
Females: | 0.85 × above value

Table 2: Recommended Dosing Schedule for Cefepime for Injection and Dextrose Injection in Adult Patients With Creatinine Clearance Less Than or Equal to 60 mL/min
Creatinine Clearance (mL/min) | Recommended Maintenance Schedule
Greater than 60 | 500 mg every 12 hours | 1 g every 12 hours | 2 g every 12 hours | 2 g every 8 hours
30–60 | 500 mg every 24 hours | 1 g every 24 hours | 2 g every 24 hours | 2 g every 12 hours
11–29 | 500 mg every 24 hours | 500 mg every 24 hours | 1 g every 24 hours | 2 g every 24 hours
Less than 11 | 250 mg every 24 hours | 250 mg every 24 hours | 500 mg every 24 hours | 1 g every 24 hours
Continuous Ambulatory Peritoneal Dialysis (CAPD) | 500 mg every 48 hours | 1 g every 48 hours | 2 g every 48 hours | 2 g every 48 hours
Hemodialysis [On hemodialysis days, Cefepime for Injection and Dextrose Injection should be administered following hemodialysis. Whenever possible, Cefepime for Injection and Dextrose Injection should be administered at the same time each day.] | 1 g on day 1, then 500 mg every 24 hours thereafter |  |  | 1 g every 24 hours

In patients undergoing Continuous Ambulatory Peritoneal Dialysis (CAPD), Cefepime for Injection and Dextrose Injection may be administered at normally recommended doses at a dosage interval of every 48 hours (see Table 2).

In patients undergoing hemodialysis, approximately 68% of the total amount of cefepime present in the body at the start of dialysis will be removed during a 3-hour dialysis period. The dosage of Cefepime for Injection and Dextrose Injection for hemodialysis patients is 1 g on Day 1 followed by 500 mg every 24 hours for the treatment of all infections except febrile neutropenia, which is 1 g every 24 hours.

Cefepime for Injection and Dextrose Injection should be administered at the same time each day and following the completion of hemodialysis on hemodialysis days (see Table 2).

Pediatric Patients

Data in pediatric patients with impaired renal function are not available; however, since cefepime pharmacokinetics are similar in adults and pediatric patients [see Clinical Pharmacology (12.3)], changes in the dosing regimen proportional to those in adults (see Tables 1 and 2) are recommended for pediatric patients.

2.4 Preparation for Use of Cefepime for Injection and Dextrose Injection in DUPLEX® Container

This reconstituted solution is for intravenous use only.

Do not use plastic containers in series connections. Such use would result in air embolism due to residual air being drawn from the primary container before administration of the fluid from the secondary container is complete. If administration is controlled by a pumping device, care must be taken to discontinue pumping action before the container runs dry or air embolism may result.

Parenteral drug products should be inspected visually for particulate matter and discoloration prior to administration. Use only if solution is clear and container and seals are intact.

DUPLEX® Container Storage

- To avoid inadvertent activation, the DUPLEX® Container should remain in the folded position until activation is intended.

Patient Labeling and Drug Powder/Diluent Inspection

- Apply patient-specific label on foil side of container. Use care to avoid activation. Do not cover any portion of foil strip with patient label.
- Unlatch side tab and unfold DUPLEX® Container (see Diagram 1).
- Visually inspect diluent chamber for particulate matter.
- Use only if container and seals are intact.
- To inspect the drug powder for foreign matter or discoloration, peel foil strip from drug chamber (see Diagram 2).
- Protect from light after removal of foil strip.
  Note: If foil strip is removed, the container should be re-folded and the side tab latched until ready to activate. The product must then be used within 7 days, but not beyond the labeled expiration date.

Reconstitution (Activation)

- Do not use directly after storage by refrigeration, allow the product to equilibrate to room temperature before patient use.
- Unfold the DUPLEX® container and point the set port in a downward direction. Starting at the hanger tab end, fold the DUPLEX® Container just below the diluent meniscus trapping all air above the fold. To activate, squeeze the folded diluent chamber until the seal between the diluent and powder opens, releasing diluent into the drug powder chamber (see Diagram 3).
- Agitate the liquid-powder mixture until the drug powder is completely dissolved.
  Note: Following reconstitution (activation), product must be used within 12 hours if stored at room temperature or within 5 days if stored under refrigeration.

Administration

- Visually inspect the reconstituted solution for particulate matter.
- Point the set port in a downwards direction. Starting at the hanger tab end, fold the DUPLEX® Container just below the solution meniscus trapping all air above the fold. Squeeze the folded DUPLEX® Container until the seal between reconstituted drug solution and set port opens, releasing liquid to set port (see Diagram 4).
- Prior to attaching the IV set, check for minute leaks by squeezing container firmly. If leaks are found, discard container and solution as sterility may be compromised.
- Using aseptic technique, peel foil cover from the set port and attach sterile administration set (see Diagram 5).
- Refer to directions for use accompanying the administration set.

Important Administration Instructions

- Do not use in series connections.
- Do not introduce additives into the DUPLEX® Container.
- Administer Cefepime for Injection and Dextrose Injection intravenously over approximately 30 minutes.
- Discard unused portions of solutions.
- Intermittent intravenous infusion with a Y-type administration set can be accomplished with compatible solutions. However, during infusion of Cefepime for Injection and Dextrose Injection, it is advisable to discontinue the other solution.
- Solutions of cefepime should not be added to solutions of ampicillin at a concentration greater than 40 mg/mL, and should not be added to metronidazole, vancomycin, gentamicin, tobramycin, netilimicin sulfate or aminophylline because of potential interaction. However, if concurrent therapy with cefepime is indicated, each of these antibacterials can be administered separately.

3 DOSAGE FORMS AND STRENGTHS

Dual-chamber, single-dose container:

- 1 g cefepime for injection USP and 50 mL of 5% dextrose injection USP
- 2 g cefepime for injection USP and 50 mL of 5% dextrose injection USP

4 CONTRAINDICATIONS

4.1 Hypersensitivity to Cefepime or the Cephalosporin Class of Antibacterials, Penicillins, or Other Beta-lactam Antibacterials

Cefepime for Injection and Dextrose Injection is contraindicated in patients who have shown immediate hypersensitivity reactions to cefepime or the cephalosporin class of antibacterial drugs, penicillins or other beta-lactam antibacterials.

4.2 Hypersensitivity to Corn Products

Solutions containing dextrose may be contraindicated in patients with hypersensitivity to corn products.

5 WARNINGS AND PRECAUTIONS

5.1 Hypersensitivity Reactions

Before therapy with Cefepime for Injection and Dextrose Injection is instituted, careful inquiry should be made to determine whether the patient has had previous immediate hypersensitivity reactions to cefepime, cephalosporins, penicillins, or other drugs. Exercise caution if this product is to be given to penicillin-sensitive patients because cross-hypersensitivity among beta-lactam antibacterials has been clearly documented and may occur in up to 10% of patients with a history of penicillin allergy. If an allergic reaction to Cefepime for Injection and Dextrose Injection occurs, discontinue the drug and institute appropriate supportive measures.

5.2 Neurotoxicity

Serious adverse reactions have been reported including life-threatening or fatal occurrences of the following: encephalopathy (disturbance of consciousness including confusion, hallucinations, stupor, and coma), aphasia, myoclonus, seizures, and nonconvulsive status epilepticus [see Adverse Reactions (6.2)]. Most cases occurred in patients with renal impairment who did not receive appropriate dosage adjustment. However, some cases of neurotoxicity occurred in patients receiving a dosage adjustment appropriate for their degree of renal impairment.
In the majority of cases, symptoms of neurotoxicity were reversible and resolved after discontinuation of cefepime and/or after hemodialysis. If neurotoxicity associated with cefepime therapy occurs, discontinue cefepime and institute appropriate supportive measures.

5.3 Clostridioides difficile-Associated Diarrhea

Clostridioides difficile-associated diarrhea (CDAD) has been reported with use of nearly all antibacterial agents, including cefepime, and may range in severity from mild diarrhea to fatal colitis. Treatment with antibacterial agents alters the normal flora of the colon leading to overgrowth of C. difficile.

C. difficile produces toxins A and B, which contribute to the development of CDAD. Hypertoxin-producing strains of C. difficile cause increased morbidity and mortality, as these infections can be refractory to antimicrobial therapy and may require colectomy. CDAD must be considered in all patients who present with diarrhea following antibacterial drug use. Careful medical history is necessary since CDAD has been reported to occur over two months after the administration of antibacterial agents.

If CDAD is suspected or confirmed, ongoing antibacterial use not directed against C. difficile may need to be discontinued. Appropriate fluid and electrolyte management, protein supplementation, antibacterial drug treatment of C. difficile, and surgical evaluation should be instituted as clinically indicated.

5.4 Risk of Development of Drug-resistant Bacteria

Prescribing Cefepime for Injection and Dextrose Injection in the absence of proven or strongly suspected bacterial infection or a prophylactic indication is unlikely to provide benefit to the patient and increases the risk of the development of drug-resistant bacteria.

As with other antimicrobials, prolonged use of Cefepime for Injection and Dextrose Injection may result in overgrowth of nonsusceptible microorganisms. Repeated evaluation of the patient's condition is essential. Should superinfection occur during therapy, appropriate measures should be taken.

5.5 Drug/Laboratory Test Interactions

Urinary Glucose

The administration of cefepime may result in a false-positive reaction with glucose in the urine when using glucose tests based on Benedict’s copper reduction reaction that determine the amount of reducing substances like glucose in the urine. It is recommended that glucose tests based on enzymatic glucose oxidase be used.

Coombs’ Test

Positive direct Coombs' tests have been reported during treatment with cefepime. In patients who develop hemolytic anemia, discontinue the drug and institute appropriate therapy. Positive Coombs' test may be observed in newborns whose mothers have received cephalosporin antibacterial drugs before parturition.

Prothrombin Time

Many cephalosporins, including cefepime, have been associated with a fall in prothrombin activity. Those at risk include patients with renal or hepatic impairment, or poor nutritional state, as well as patients receiving a protracted course of antimicrobial therapy. Prothrombin time should be monitored in patients at risk, and exogenous vitamin K administered as indicated.

5.6 Patients with a History of Gastrointestinal Disease

Cefepime for Injection and Dextrose Injection should be prescribed with caution in individuals with a history of gastrointestinal disease, particularly colitis.

5.7 Possible Effects of Arginine on Glucose Metabolism

Cefepime for Injection and Dextrose Injection contains arginine. Arginine has been shown to alter glucose metabolism and elevate serum potassium transiently when administered at 33 times the amount provided by the maximum recommended human dose of cefepime. The effect of lower doses is not presently known.

5.8 Patients with Overt or Known Subclinical Diabetes Mellitus or Carbohydrate Intolerance

As with other dextrose-containing solutions, Cefepime for Injection and Dextrose Injection should be prescribed with caution in patients with overt or known subclinical diabetes mellitus or carbohydrate intolerance for any reason.

6 ADVERSE REACTIONS

The following adverse reactions are discussed in other sections of the labeling:

- Hypersensitivity reactions [see Warnings and Precautions (5.1)]
- Neurotoxicity [see Warnings and Precautions (5.2)]
- Clostridioides difficile-associated diarrhea [see Warnings and Precautions (5.3)]

6.1 Clinical Trials Experience

Because clinical trials are conducted under widely varying conditions, adverse reaction rates observed in the clinical trials of a drug cannot be directly compared to rates in the clinical trials of another drug and may not reflect the rates observed in practice.

In clinical trials using multiple doses of cefepime, 4137 patients were treated with the recommended dosages of cefepime (500 mg to 2 g intravenously every 12 hours). There were no deaths or permanent disabilities thought related to drug toxicity. Sixty-four (1.5%) patients discontinued medication due to adverse reactions thought by the investigators to be possibly, probably, or almost certainly related to drug toxicity. Thirty-three (51%) of these sixty-four patients who discontinued therapy did so because of rash. The percentage of cefepime-treated patients who discontinued study drug because of drug-related adverse reactions was similar at daily doses of 500 mg, 1 g, and 2 g every 12 hours (0.8%, 1.1%, and 2.0%, respectively). However, the incidence of discontinuation due to rash increased with the higher recommended doses.

The following adverse reactions (Table 3) were identified in clinical trials conducted in North America (n=3125 cefepime-treated patients).

Table 3: Adverse Clinical Reactions Cefepime Multiple-dose Dosing Regimens Clinical Trials – North America
Incidence equal to or greater than 1% | Local adverse reactions (3%), including phlebitis (1.3%), pain and/or inflammation (0.6%) [Local reactions, irrespective of relationship to cefepime in those patients who received intravenous infusion (n=3048).] ; rash (1.1%)
Incidence less than 1% but greater than 0.1% | Colitis (including pseudomembranous colitis), diarrhea, erythema, fever, headache, nausea, oral moniliasis, pruritus, urticaria, vaginitis, vomiting, anemia

At the higher dose of 2 g every 8 hours, the incidence of probably-related adverse reactions was higher among the 795 patients who received this dose of cefepime. Reactions included rash (4%), diarrhea (3%), nausea (2%), vomiting (1%), pruritus (1%), fever (1%), and headache (1%).

The following (Table 4) adverse laboratory changes, irrespective of relationship to therapy with cefepime, were seen during clinical trials conducted in North America.

Table 4: Adverse Laboratory Changes Cefepime Multiple-dose Dosing Regimens Clinical Trials – North America
Incidence equal to or greater than 1% | Positive Coombs' Test (without hemolysis) (16.2%); decreased phosphorus (2.8%); increased Alanine Transaminase (ALT) (2.8%), Aspartate Transaminase (AST) (2.4%); eosinophils (1.7%); abnormal PTT (1.6%), Prothrombin Time PT (1.4%)
Incidence less than 1% but greater than 0.1% | Increased alkaline phosphatase, Blood Urea Nitrogen (BUN), calcium, creatinine, phosphorus, potassium, total bilirubin; decreased calcium [Hypocalcemia was more common among elderly patients. Clinical consequences from changes in either calcium or phosphorus were not reported.] , hematocrit, neutrophils, platelets, White Blood Cells (WBC)

A similar safety profile was seen in clinical trials of pediatric patients.

6.2 Postmarketing Experience

The following adverse reactions have been reported during postapproval use of cefepime. Because these reactions are reported voluntarily from a population of uncertain size, it is not always possible to readily estimate their frequency or establish a causal relationship to drug exposure.

In addition to the adverse reactions reported during the North American clinical trials with cefepime, the following adverse reactions have been reported during worldwide postmarketing experience. Encephalopathy (disturbance of consciousness including confusion, hallucinations, stupor, and coma), aphasia, myoclonus, seizures, and nonconvulsive status epilepticus have been reported [see Warnings and Precautions (5.2)].

Anaphylaxis (including anaphylactic shock, transient leukopenia, neutropenia, agranulocytosis and thrombocytopenia) has been reported.

6.3 Cephalosporin-class Adverse Reactions

In addition to the adverse reactions listed above that have been observed in patients treated with cefepime, the following adverse reactions and altered laboratory tests have been reported for cephalosporin-class antibacterials:

Stevens-Johnson syndrome, erythema multiforme, toxic epidermal necrolysis, renal impairment, toxic nephropathy, aplastic anemia, hemolytic anemia, hemorrhage, hepatic impairment including cholestasis, and pancytopenia.

7 DRUG INTERACTIONS

7.1 Drug/Laboratory Test Interactions

The administration of Cefepime for Injection and Dextrose Injection may result in a false-positive reaction for glucose in the urine with certain methods. It is recommended that glucose tests based on enzymatic glucose oxidase reactions be used.

7.2 Aminoglycosides

Monitor renal function if aminoglycosides are to be administered with Cefepime for Injection and Dextrose Injection because of the increased potential of nephrotoxicity and ototoxicity of aminoglycoside antibacterials.

7.3 Diuretics

Nephrotoxicity has been reported following concomitant administration of cephalosporins with potent diuretics such as furosemide. Monitor renal function when cefepime is concomitantly administered with potent diuretics.

8 USE IN SPECIFIC POPULATIONS

8.1 Pregnancy

Risk Summary

There are no cases of cefepime exposure during pregnancy reported from postmarketing experience or from clinical trials. Available data from published observational studies and case reports over several decades with cephalosporin use in pregnant women have not established drug-associated risks of major birth defects, miscarriage or adverse maternal or fetal outcomes (see Data). Cefepime crosses the placenta.

Cefepime was not associated with adverse developmental outcomes in rats, mice, or rabbits when administered parenterally during organogenesis. The doses used in these studies were 1.6 times (rats), approximately equal to (mice) and 0.3 times (rabbits) the maximum recommended human dose (see Data).

The estimated background risk of major birth defects and miscarriage for the indicated population is unknown. All pregnancies have a background risk of birth defect, loss, or other adverse outcomes. In the U.S. general population, the estimated background risk of major birth defects and miscarriage in clinically recognized pregnancies is 2 to 4% and 15 to 20%, respectively.

Data

Human Data

While available studies cannot definitively establish the absence of risk, published data from case-control studies and case reports over several decades have not identified an association with cephalosporin use during pregnancy and major birth defects, miscarriage, or other adverse maternal or fetal outcomes. Available studies have methodologic limitations, including small sample size, retrospective data collection, and inconsistent comparator groups.

Animal Data

Cefepime was not embryocidal and did not cause fetal malformations when administered parenterally during the period of organogenesis to rats at doses up to 1000 mg/kg/day, to mice at doses up to 1200 mg/kg/day, or to rabbits at doses up to 100 mg/kg/day. These doses are 1.6 times (rats), approximately equal to (mice), and 0.3 times (rabbits) the maximum recommended clinical dose based on body surface area.

8.2 Lactation

Risk Summary

Cefepime is present in human milk at low concentration (approximately 0.5 mcg/mL), following a single intravenous dose of 1000 mg. A nursing infant consuming approximately 1000 mL of human milk per day would receive approximately 0.5 mg of cefepime per day (see Data). There is no information regarding effects of cefepime on the breastfed infant or on milk production.

The developmental and health benefits of breastfeeding should be considered along with the mother’s clinical need for cefepime for injection and dextrose injection and any potential adverse effects on the breastfed child from cefepime for injection and dextrose injection or from the underlying maternal condition.

8.4 Pediatric Use

The safety and effectiveness of Cefepime for Injection and Dextrose Injection in the treatment of uncomplicated and complicated urinary tract infections (including pyelonephritis), uncomplicated skin and skin structure infections, pneumonia, and as empiric therapy for febrile neutropenic patients have been established in the age groups 2 months up to 16 years. Use of Cefepime for Injection and Dextrose Injection in these age groups is supported by evidence from adequate and well-controlled studies of cefepime in adults with additional pharmacokinetic and safety data from pediatric trials [see Clinical Pharmacology (12.3)].

Safety and effectiveness in pediatric patients below the age of 2 months have not been established. There are insufficient clinical data to support the use of Cefepime for Injection and Dextrose Injection in pediatric patients for the treatment of serious infections in the pediatric population where the suspected or proven pathogen is Haemophilus influenzae type b. In those patients in whom meningeal seeding from a distant infection site or in whom meningitis is suspected or documented, an alternate agent with demonstrated clinical efficacy in this setting should be used.

Cefepime for Injection and Dextrose Injection in the DUPLEX® Container should be used only in pediatric patients who require the entire 1 or 2 gram dose and not any fraction thereof.

8.5 Geriatric Use

Of the more than 6400 adults treated with cefepime in clinical studies, 35% were 65 years or older while 16% were 75 years or older. When geriatric patients received the usual recommended adult dose, clinical efficacy and safety were comparable to clinical efficacy and safety in nongeriatric
adult patients.

Serious adverse reactions have occurred in geriatric patients with renal impairment given unadjusted doses of cefepime, including life-threatening or fatal occurrences of the following: encephalopathy, myoclonus, and seizures [see Warnings and Precautions (5.2), Adverse Reactions (6.2)].

This drug is known to be substantially excreted by the kidney, and the risk of toxic reactions to this drug may be greater in patients with impaired renal function. Because elderly patients are more likely to have decreased renal function, care should be taken in dose selection, and renal function should be monitored [see Clinical Pharmacology (12.3), Warnings and Precautions (5.2), and Dosage and Administration (2.3)].

8.6 Renal Impairment

Adjust the dose of Cefepime Injection in patients with creatinine clearance less than or equal to 60 mL/min to compensate for the slower rate of renal elimination [see Dosage Adjustments in Patients with Renal Impairment (2.3)].

10 OVERDOSAGE

Patients who receive an overdose should be carefully observed and given supportive treatment. In the presence of renal impairment, hemodialysis, not peritoneal dialysis, is recommended to aid in the removal of cefepime from the body. Accidental overdosing has occurred when large doses were given to patients with impaired renal function. Symptoms of overdose include encephalopathy (disturbance of consciousness including confusion, hallucinations, stupor, and coma), myoclonus, seizures, nonconvulsive status epilepticus, and neuromuscular excitability [see Warnings and Precautions (5.2), Adverse Reactions (6.2), and Dosage and Administration (2.3)].

11 DESCRIPTION

Cefepime hydrochloride, USP is a semi-synthetic, broad spectrum, cephalosporin antibacterial for parenteral administration. The chemical name is 1-[[(6R,7R)-7-[2-(2-amino-4-thiazolyl)-glyoxylamido]-2-carboxy-8-oxo-5-thia-1-azabicyclo[4.2.0]oct-2-en-3-yl]methyl]-1-methylpyrrolidinium chloride, 7^2-(Z)-(O-methyloxime), monohydrochloride, monohydrate, which corresponds to the following structural formula:

Cefepime hydrochloride (monohydrate) has a molecular mass of 571.50 and a molecular formula of C19H25ClN6O5S2•HCl•H2O.

Cefepime hydrochloride is a white to pale yellow powder. Cefepime hydrochloride contains the equivalent of not less than 825 mcg and not more than 911 mcg of cefepime (C19H24N6O5S2) per mg, calculated on an anhydrous basis. It is highly soluble in water.

Cefepime for Injection USP and Dextrose Injection USP in the DUPLEX® dual chamber container is supplied for intravenous administration in strengths equivalent to 1 g and 2 g of cefepime. Cefepime for Injection USP and Dextrose Injection USP is supplied as a sterile, nonpyrogenic, single-dose packaged combination of cefepime hydrochloride with L-arginine (drug chamber) and 50 mL of 5% dextrose injection (diluent) in the DUPLEX® sterile container.

The powder chamber of the DUPLEX® container contains a sterile, dry mixture of cefepime hydrochloride and L-arginine. It contains the equivalent of not less than 90.0 percent and not more than 115.0 percent of the labeled amount of cefepime (C19H24N6O5S2). The L-arginine, at an approximate concentration of 725 mg/g of cefepime, is added to control the pH of the reconstituted solution at 4.0 – 6.0.

The diluent chamber contains Dextrose Injection USP, an iso-osmotic diluent using Hydrous Dextrose USP in Water for Injection USP. Dextrose Injection USP is sterile, nonpyrogenic, and contains no bacteriostatic or antimicrobial agents. Its empirical formula is C6H12O6•H2O and its molecular weight is 198.17.

Hydrous Dextrose USP has the following structural (molecular) formula:

The DUPLEX® container is a flexible dual chamber container. After removing the peelable foil strip, activating the seals, and thoroughly mixing, the reconstituted drug product is hyperosmotic and is intended for single intravenous use. Each 50 mL contains cefepime hydrochloride equivalent to either 1 gram or 2 grams of cefepime. Reconstituted solutions of Cefepime for Injection USP and Dextrose Injection USP range in color from colorless to amber.

The DUPLEX® dual chamber container is made from a specially formulated material. The product (diluent and drug) contact layer is a mixture of thermoplastic rubber and a polypropylene ethylene copolymer that contains no plasticizers. The safety of the container is supported by USP biological evaluation procedures.

12 CLINICAL PHARMACOLOGY

12.1 Mechanism of Action

Cefepime is a cephalosporin antibacterial drug [see Microbiology (12.4)].

12.2 Pharmacodynamics

Similar to other beta-lactam antimicrobial agents, the time that the unbound plasma concentration of cefepime exceeds the MIC of the infecting organism has been shown to best correlate with efficacy in animal models of infection. However, the pharmacokinetic/pharmacodynamic relationship for cefepime has not been evaluated in patients.

12.3 Pharmacokinetics

Pharmacokinetic parameters for cefepime in healthy adult male volunteers (n=9) following single 30-minute IV infusions of cefepime 500 mg, 1 g, and 2 g are summarized in Table 5. Elimination of cefepime is principally via renal excretion with an average (±SD) half-life of 2 (±0.3) hours and total body clearance of 120 (±8) mL/min in healthy volunteers. Cefepime pharmacokinetics are linear over the range 250 mg to 2 g. There is no evidence of accumulation in healthy adult male volunteers (n=7) receiving clinically relevant doses for a period of 9 days.

Table 5: Mean Pharmacokinetic Parameters for Cefepime (±SD), Intravenous Administration
Parameter | 500 mg IV | 1 g IV | 2 g IV
Cmax, mcg/mL | 39.1 (3.5) | 81.7 (5.1) | 163.9 (25.3)
AUC, h∙mcg/mL | 70.8 (6.7) | 148.5 (15.1) | 284.8 (30.6)
Number of subjects (male) | 9 | 9 | 9

Distribution

The average steady-state volume of distribution of cefepime is 18.0 (±2.0) L. The serum protein binding of cefepime is approximately 20% and is independent of its concentration in serum.

Concentrations of cefepime achieved in specific tissues and body fluids are listed in Table 6.

Table 6: Mean Concentrations of Cefepime in Specific Body Fluids (mcg/mL) or Tissues (mcg/g)
Tissue or Fluid | Dose/Route | # of Patients | Average Time of Sample Post-Dose (h) | Average Concentration
Blister Fluid | 2 g IV | 6 | 1.5 | 81.4 mcg/mL
Bronchial Mucosa | 2 g IV | 20 | 4.8 | 24.1 mcg/g
Sputum | 2 g IV | 5 | 4 | 7.4 mcg/mL
Urine | 500 mg IV | 8 | 0–4 | 292 mcg/mL
 | 1 g IV | 12 | 0–4 | 926 mcg/mL
 | 2 g IV | 12 | 0–4 | 3120 mcg/mL
Bile | 2 g IV | 26 | 9.4 | 17.8 mcg/mL
Peritoneal Fluid | 2 g IV | 19 | 4.4 | 18.3 mcg/mL
Appendix | 2 g IV | 31 | 5.7 | 5.2 mcg/g
Gallbladder | 2 g IV | 38 | 8.9 | 11.9 mcg/g
Prostate | 2 g IV | 5 | 1 | 31.5 mcg/g

Data suggest that cefepime does cross the inflamed blood-brain barrier. The clinical relevance of these data are uncertain at this time.

Metabolism and Excretion

Cefepime is metabolized to N-methylpyrrolidine (NMP), which is rapidly converted to the N-oxide (NMP-N-oxide). Urinary recovery of unchanged cefepime accounts for approximately 85% of the administered dose. Less than 1% of the administered dose is recovered from urine as NMP, 6.8% as NMP-N-oxide, and 2.5% as an epimer of cefepime. Because renal excretion is a significant pathway of elimination, patients with renal dysfunction and patients undergoing hemodialysis require dosage adjustment [see Dosage and Administration (2.3)].

Specific Populations

Patients with Renal Impairment

Cefepime pharmacokinetics have been investigated in patients with various degrees of renal impairment (n=30). The average half-life in patients requiring hemodialysis was 13.5 (±2.7) hours and in patients requiring continuous peritoneal dialysis was 19 (±2.0) hours. Cefepime total body clearance decreased proportionally with creatinine clearance in patients with abnormal renal function, which serves as the basis for dosage adjustment recommendations in this group of patients [see Dosage and Administration (2.3)].

Patients with Hepatic Impairment

The pharmacokinetics of cefepime were unaltered in patients with hepatic impairment who received a single 1 g dose (n=11).

Geriatric Patients

Cefepime pharmacokinetics have been investigated in elderly (65 years of age and older) men (n=12) and women (n=12) whose mean (SD) creatinine clearance was 74.0 (±15) mL/min. There appeared to be a decrease in cefepime total body clearance as a function of creatinine clearance. Therefore, dosage administration of cefepime in the elderly should be adjusted as appropriate if the patient's creatinine clearance is 60 mL/min or less [see Dosage and Administration (2.3)].

Pediatric Patients

Cefepime pharmacokinetics have been evaluated in pediatric patients from 2 months to 11 years of age following single and multiple doses on every 8 hours (n=29) and every 12 hours (n=13) schedules. Following a single intravenous dose, total body clearance and the steady-state volume of distribution averaged 3.3 (±1) mL/min/kg and 0.3 (±0.1) L/kg, respectively. The urinary recovery of unchanged cefepime was 60.4 (±30.4)% of the administered dose, and the average renal clearance was 2 (±1.1) mL/min/kg. There were no significant effects of age or gender (25 male vs. 17 female) on total body clearance or volume of distribution, corrected for body weight. No accumulation was seen when cefepime was given at 50 mg per kg every 12 hours (n=13), while Cmax, AUC, and t1/2 were increased about 15% at steady state after 50 mg per kg every 8 hours. The exposure to cefepime following a 50 mg per kg intravenous dose in a pediatric patient is comparable to that in an adult treated with a 2 g intravenous dose. The absolute bioavailability of cefepime after an intramuscular dose of 50 mg per kg was 82.3 (±15)% in eight patients.

12.4 Microbiology

Mechanism of Action

Cefepime is a bactericidal agent that acts by inhibition of bacterial cell wall synthesis. Cefepime has a broad spectrum of in vitro activity that encompasses a wide range of Gram-positive and Gram-negative bacteria. Within bacterial cells, the molecular targets of cefepime are the penicillin binding proteins (PBP).

Antimicrobial Activity

Cefepime has been shown to be active against most isolates of the following microorganisms, both in vitro and in clinical infections [see Indications and Usage (1)]:

- Gram-negative bacteria:
  - Enterobacter spp.
  - Escherichia coli
  - Klebsiella pneumoniae
  - Proteus mirabilis
  - Pseudomonas aeruginosa

- Gram-positive Bacteria:
  - Staphylococcus aureus (methicillin-susceptible isolates only)
  - Streptococcus pneumoniae
  - Streptococcus pyogenes
  - Viridans group streptococci

The following in vitro data are available, but their clinical significance is unknown. At least 90 percent of the following bacteria exhibit an in vitro minimum inhibitory concentration (MIC) less than or equal to the susceptible breakpoint for cefepime against isolates of similar genus or organism group. However, the efficacy of cefepime in treating clinical infections due to these bacteria has not been established in adequate and well-controlled clinical trials.

- Gram-positive bacteria:
  - Staphylococcus epidermidis (methicillin-susceptible isolates only)
  - Staphylococcus saprophyticus
  - Streptococcus agalactiae

NOTE: Most isolates of enterococci e.g., Enterococcus faecalis and methicillin-resistant staphylococci are resistant to cefepime.

- Gram-negative bacteria:
  - Acinetobacter calcoaceticus subsp. lwoffii
  - Citrobacter diversus
  - Citrobacter freundii
  - Enterobacter agglomerans
  - Haemophilus infuenzae
  - Hafnia alvei
  - Klebsiella oxytoca
  - Moraxella catarrhalis
  - Morganella morganii
  - Proteus vulgaris
  - Providencia rettgeri
  - Providencia stuartii
  - Serratia marcescens

NOTE: Cefepime is inactive against many isolates of Stenotrophomonas maltophilia.

Susceptibility Testing

For specific information regarding susceptibility test interpretive criteria, and associated test methods and quality control standards recognized by FDA for this drug, please see: http://www.fda.gov/STIC.

13 NONCLINICAL TOXICOLOGY

13.1 Carcinogenesis, Mutagenesis, Impairment of Fertility

No animal carcinogenicity studies have been conducted with cefepime. In chromosomal aberration studies, cefepime was positive for clastogenicity in primary human lymphocytes, but negative in Chinese hamster ovary cells. In other in vitro assays (bacterial and mammalian cell mutation, DNA repair in primary rat hepatocytes, and sister chromatid exchange in human lymphocytes), cefepime was negative for genotoxic effects. Moreover, in vivo assessments of cefepime in mice (2 chromosomal aberration and 2 micronucleus studies) were negative for clastogenicity. No untoward effects on fertility were observed in rats when cefepime was administered subcutaneously at doses up to 1000 mg/kg/day (1.6 times the recommended maximum human dose based on body surface area).

14 CLINICAL STUDIES

14.1 Febrile Neutropenic Patients

The safety and efficacy of empiric cefepime monotherapy of febrile neutropenic patients have been assessed in two multicenter, randomized trials comparing cefepime monotherapy (at a dose of 2 g intravenously every 8 hours) to ceftazidime monotherapy (at a dose of 2 g intravenously every 8 hours). These studies comprised 317 evaluable patients. Table 7 describes the characteristics of the evaluable patient population.

Table 7: Demographics of Evaluable Patients (First Episodes Only)
 | Cefepime | Ceftazidime
Total | n=164 | n=153
Median age (yr) | 56 (range, 18 to 82) | 55 (range, 16 to 84)
Male | 86 (52%) | 85 (56%)
Female | 78 (48%) | 68 (44%)
Leukemia | 65 (40%) | 52 (34%)
Other hematologic malignancies | 43 (26%) | 36 (24%)
Solid tumor | 54 (33%) | 56 (37%)
Median ANC nadir (cells/microliter) | 20 (range, 0 to 500) | 20 (range, 0 to 500)
Median duration of neutropenia (days) | 6 (range, 0 to 39) | 6 (range, 0 to 32)
Indwelling venous catheter | 97 (59%) | 86 (56%)
Prophylactic antibacterial drugs | 62 (38%) | 64 (42%)
Bone marrow graft | 9 (5%) | 7 (5%)
SBP less than 90 mm Hg at entry | 7 (4%) | 2 (1%)
ANC = absolute neutrophil count; SBP = systolic blood pressure

Table 8 describes the clinical response rates observed. For all outcome measures, cefepime was therapeutically equivalent to ceftazidime.

Table 8: Pooled Response Rates for Empiric Therapy of Febrile Neutropenic Patients
 | % Response
Outcome Measures | Cefepime (n=164) | Ceftazidime (n=153)
Primary episode resolved with no treatment modification, no new febrile episodes or infection, and oral antibacterial drugs allowed for completion of treatment | 51 | 55
Primary episode resolved with no treatment modification, no new febrile episodes or infection and no post-treatment oral antibacterial drugs | 34 | 39
Survival, any treatment modification allowed | 93 | 97
Primary episode resolved with no treatment modification and oral antibacterial drugs allowed for completion of treatment | 62 | 67
Primary episode resolved with no treatment modification and no post-treatment oral antibacterial drugs | 46 | 51

Insufficient data exist to support the efficacy of cefepime monotherapy in patients at high risk for severe infection (including patients with a history of recent bone marrow transplantation, with hypotension at presentation, with an underlying hematologic malignancy, or with severe or prolonged neutropenia). No data are available in patients with septic shock.

14.2 Complicated Intra-abdominal Infections

Patients hospitalized with complicated intra-abdominal infections participated in a randomized, double-blind, multicenter trial comparing the combination of cefepime (2 g every 12 hours) plus intravenous metronidazole (500 mg every 6 hours) versus imipenem/cilastatin (500 mg every 6 hours) for a maximum duration of 14 days of therapy. The study was designed to demonstrate equivalence of the two therapies. The primary analyses were conducted on the protocol-valid population, which consisted of those with a surgically confirmed complicated infection, at least one pathogen isolated pretreatment, at least 5 days of treatment, and a 4 to 6 week follow-up assessment for cured patients. Subjects in the imipenem/cilastatin arm had higher APACHE II scores at baseline. The treatment groups were otherwise generally comparable with regard to their pretreatment characteristics. The overall clinical cure rate among the protocol-valid patients was 81% (51 cured/63 evaluable patients) in the cefepime plus metronidazole group and 66% (62/94) in the imipenem/cilastatin group. The observed differences in efficacy may have been due to a greater proportion of patients with high APACHE II scores in the imipenem/cilastatin group.

15 REFERENCES

1. Cockcroft DW, Gault MH. Prediction of creatinine clearance from serum creatinine. Nephron. 1976; 16:31–41.

16 HOW SUPPLIED/STORAGE AND HANDLING

Cefepime for Injection USP and Dextrose Injection USP in the DUPLEX® Container is a flexible dual chamber container supplied in two strengths, 1 and 2 g cefepime. The diluent chamber contains approximately 50 mL of 5% Dextrose Injection.

Cefepime for Injection USP and Dextrose Injection USP is supplied sterile and nonpyrogenic in the DUPLEX Container packaged 24 single-dose units per case.

NDC | REF | Dose | Volume
0264-3193-11 | 3193-11 | 1 g | 50 mL
0264-3195-11 | 3195-11 | 2 g | 50 mL

Store the unactivated unit at 20–25°C (68–77°F). Excursions permitted to 15–30°C (59–86°F). [See USP Controlled Room Temperature.] Do not freeze.

Not made with natural rubber latex, PVC or Di(2-ethylhexyl)phthalate (DEHP).

As with other cephalosporins, reconstituted Cefepime for Injection USP and Dextrose Injection USP tends to darken depending on storage conditions, within the stated recommendations. However, product potency is not adversely affected.

Use only if prepared solution is clear and free from particulate matter.

17 PATIENT COUNSELING INFORMATION

Allergic Reactions

Advise patients that allergic reactions, including serious allergic reactions could occur and that serious reactions require immediate treatment and discontinuation of cefepime. Patients should report to their health care provider any previous allergic reactions to cefepime, cephaloposrins, penicillins, or other similar antibacterial drugs [see Warnings and Precautions (5.1)].

Neurotoxicity

Advise patients of neurological adverse events that could occur with Cefepime for Injection and Dextrose Injection use. Instruct patients or their caregivers to inform their healthcare provider at once of any neurological signs and symptoms, including encephalopathy (disturbance of consciousness including confusion, hallucinations, stupor, and coma), aphasia (disturbance of speaking and understanding spoken and written language), myoclonus, seizures and nonconvulsive status epilepticus, for immediate treatment, dosage adjustment, or discontinuation of Cefepime for Injection and Dextrose Injection [see Warnings and Precautions (5.2)].

Diarrhea

Diarrhea is a common problem caused by antibacterial drugs, which usually ends when the antibacterial drug is discontinued. Inform patient that they may develop watery and bloody stools (with or without stomach cramps and fever) during the treatment and as late as two or more months after having taken the last dose of the antibacterial drug. Inform patients that they should contact their physician as soon as possible if this occurs [see Warnings and Precautions (5.3)].

Antibacterial Resistance

Patients should be counseled that antibacterial drugs including Cefepime for Injection and Dextrose Injection should only be used to treat bacterial infections. They do not treat viral infections (e.g., the common cold). When Cefepime for Injection and Dextrose Injection is prescribed to treat a bacterial infection, patients should be told that although it is common to feel better early in the course of therapy, the medication should be taken exactly as directed. Skipping doses or not completing the full course of therapy may (1) decrease the effectiveness of the immediate treatment and (2) increase the likelihood that bacteria will develop resistance and will not be treatable by Cefepime for Injection and Dextrose Injection or other antibacterial drugs in the future.

B. Braun Medical Inc.
Bethlehem, PA 18018-3524 USA
1-800-227-2862
Prepared in USA.
API from USA and Brazil.

DUPLEX is a registered trademark of B. Braun Medical Inc.
Apache is a registered trademark of Cerner Innovation, Inc.

Rx only

Y36-003-023 LD-107-8

PRINCIPAL DISPLAY PANEL - 1g / 50 mL Container Label

Cefepime for Injection USP
and Dextrose Injection USP
1g*

REF 3193-11
NDC 0264-3193-11

DUPLEX® CONTAINER

50 mL

Use only after mixing contents of both chambers.

For IV Use Only Hyperosmotic Single-Dose Sterile/Nonpyrogenic

* Contains sterile Cefepime Hydrochloride USP equivalent to 1 g of cefepime and
L-arginine for pH adjustment.

After reconstitution each 50 mL single-dose unit contains: Cefepime for Injection
(equivalent to 1 g cefepime) with approximately 2.83 g (5% w/v) Hydrous Dextrose USP in
Water for Injection USP. Approximate osmolality: 431 mOsmol/kg

Prior to Reconstitution: Store at 20-25°C (68-77°F). Excursions permitted to 15-30°C
(59-86°F) [See USP Controlled Room Temperature.] Use only if container and seals are
intact. Do not peel foil strip until ready for use. After foil strip removal, product must be
used within 7 days, but not beyond the labeled expiration date. Protect from light after
removal of foil strip.

Reconstitution: Hold container with set port in a downward direction and fold the
diluent chamber just below the solution meniscus. To activate seal, squeeze folded
diluent chamber until seal between diluent and drug chamber opens, releasing diluent
into drug chamber. Agitate the reconstituted solution until the drug powder is
completely dissolved. Fold the container a second time and squeeze until seal
between drug chamber and set port opens.

After Reconstitution: Use only if prepared solution is clear and free from particulate
matter. Use within 12 hours if stored at room temperature or within 5 days if stored
under refrigeration. Do not use in a series connection. Do not introduce additives into
this container. Prior to administration check for minute leaks by squeezing container
firmly. If leaks are found, discard container and solution as sterility may be impaired.
See package insert for complete directions for reconstitution and administration. Do
not freeze. Discard unused portion.

Not made with natural rubber latex, PVC or DEHP.
Rx only

B. Braun Medical Inc.
Bethlehem, PA 18018-3524

Y37-002-579
LD-210-7

EXP
LOT

Prepared in USA. API from USA and Brazil.

PRINCIPAL DISPLAY PANEL - 2g / 50mL Container Label

Cefepime for Injection USP
and Dextrose Injection USP
2g*

REF 3195-11
NDC 0264-3195-11

DUPLEX® CONTAINER

50 mL

Use only after mixing contents of both chambers.

For IV Use Only Hyperosmotic Single-Dose Sterile/Nonpyrogenic

* Contains sterile Cefepime Hydrochloride USP equivalent to 2 g of cefepime and
L-arginine for pH adjustment.

After reconstitution each 50 mL single-dose unit contains: Cefepime for Injection
(equivalent to 2 g cefepime) with approximately 2.83 g (5% w/v) Hydrous Dextrose
USP in Water for Injection USP. Approximate osmolality: 577 mOsmol/kg

Prior to Reconstitution: Store at 20-25°C (68-77°F). Excursions permitted to 15-30°C
(59-86°F) [See USP Controlled Room Temperature.] Use only if container and seals are
intact. Do not peel foil strip until ready for use. After foil strip removal, product must
be used within 7 days, but not beyond the labeled expiration date. Protect from light
after removal of foil strip.

Reconstitution: Hold container with set port in a downward direction and fold the
diluent chamber just below the solution meniscus. To activate seal, squeeze folded
diluent chamber until seal between diluent and drug chamber opens, releasing diluent
into drug chamber. Agitate the reconstituted solution until the drug powder is
completely dissolved. Fold the container a second time and squeeze until seal
between drug chamber and set port opens.

After Reconstitution: Use only if prepared solution is clear and free from particulate
matter. Use within 12 hours if stored at room temperature or within 5 days if stored
under refrigeration. Do not use in a series connection. Do not introduce additives into
this container. Prior to administration check for minute leaks by squeezing container
firmly. If leaks are found, discard container and solution as sterility may be impaired.
See package insert for complete directions for reconstitution and administration. Do
not freeze. Discard unused portion.

Not made with natural rubber latex, PVC or DEHP.
Rx only

B. Braun Medical Inc.
Bethlehem, PA 18018-3524

Y37-002-580
LD-211-7

EXP
LOT

Prepared in USA. API from USA and Brazil.

PACKAGE LABEL

Display Panel - Drug Chamber Barrier

PEEL HERE

Drug Chamber

Discard unit if foil strip is damaged. Peel foil strip only when
ready for use. Visually inspect drug prior to reconstitution.

See package insert for complete directions for reconstitution
and administration.

LD-336-1
X27-001-485